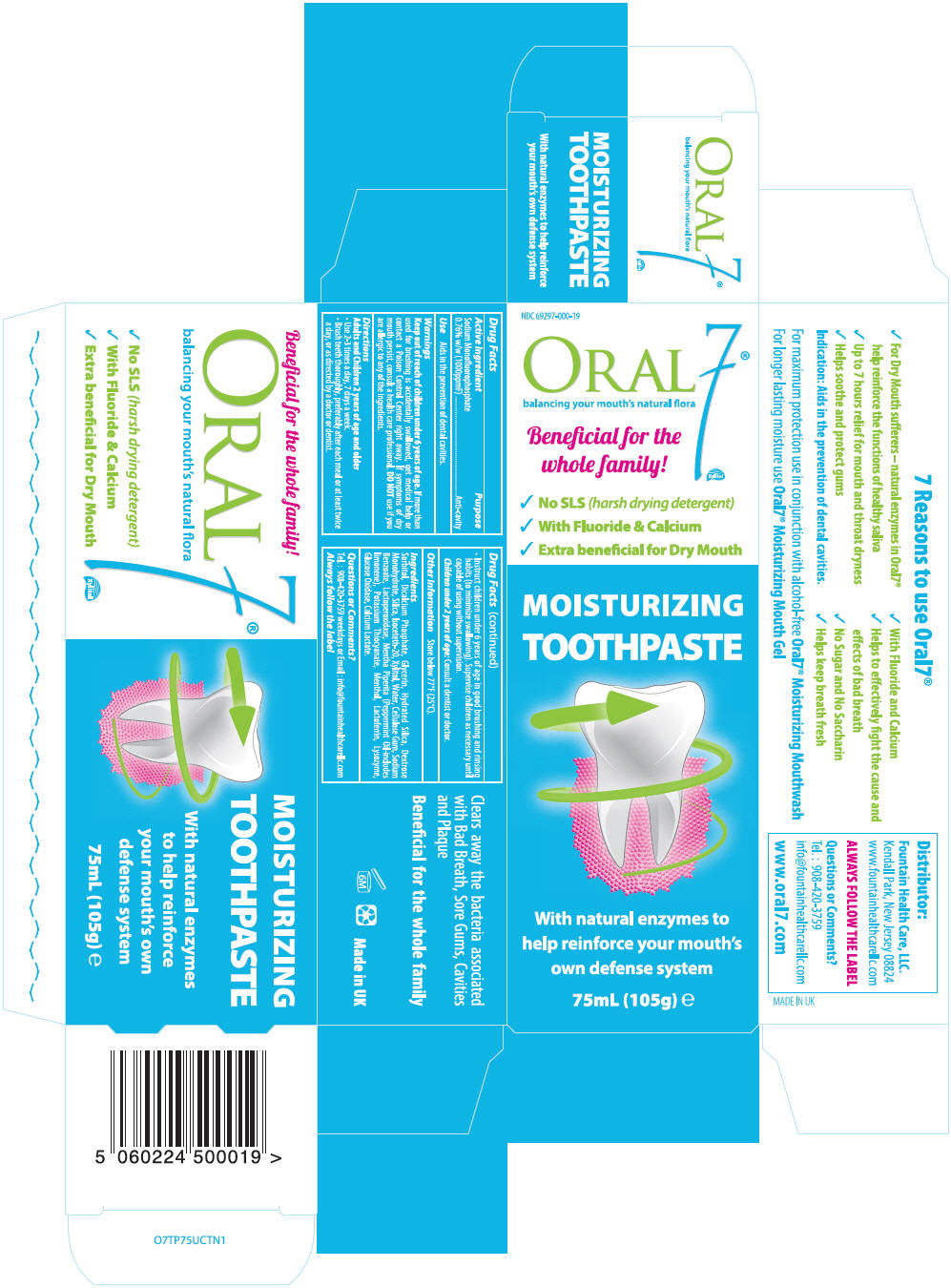 DRUG LABEL: Oral7
NDC: 69297-000 | Form: PASTE
Manufacturer: JCEC Company, Inc.
Category: otc | Type: HUMAN OTC DRUG LABEL
Date: 20150108

ACTIVE INGREDIENTS: SODIUM MONOFLUOROPHOSPHATE 1.4 mg/1 g
INACTIVE INGREDIENTS: SORBITOL; CALCIUM PHOSPHATE, DIBASIC, ANHYDROUS; GLYCERIN; HYDRATED SILICA; DEXTROSE MONOHYDRATE; SILICON DIOXIDE; ISOCETETH-20; XYLITOL; WATER; CARBOXYMETHYLCELLULOSE SODIUM; SODIUM BENZOATE; MYELOPEROXIDASE; MENTHA PIPERITA; POTASSIUM THIOCYANATE; MENTHOL, UNSPECIFIED FORM; LACTOFERRIN, BOVINE; LYSOZYME; GLUCOSE OXIDASE; CALCIUM LACTATE

Oral7®

Drug Facts

Active Ingredient

Sodium Monofluorophosphate 0.76% w/w (1000ppmF)

Purpose

Anti-cavity

Use

Aids in the prevention of dental cavities.

Warnings

Keep out of reach of children under 6 years of age. If more than used for brushing is accidentally swallowed, get medical help or contact a Poison Control Center right away. If symptoms of dry mouth persist, consult a health care professional.

DO NOT use if you are allergic to any of the ingredients.

Directions

Adults and Children 2 years of age and older

- Use 2-3 times a day, 7 days a week.
- Brush teeth thoroughly, preferably after each meal or at least twice a day, or as directed by a doctor or dentist
- Instruct children under 6 years of age in good brushing and rinsing habits (to minimize swallowing). Supervise children as necessary until capable of using without supervision.

Children under 2 years of age: Consult a dentist or doctor.

Other Information

Store below 77°F (25°C).

Ingredients

Sorbitol, Dicalcium Phosphate, Glycerin, Hydrated Silica, Dextrose Monohydrate, Silica, Isoceteth-20, Xylitol, Water, Cellulose Gum, Sodium Benzoate, Lactoperoxidase , Mentha Piperita (Peppermint Oil-includes limonene), Potassium Thiocyanate, Menthol, Lactoferrin , Lysozyme, Glucose Oxidase, Calcium Lactate

Questions or Comments?

Call Tel. : 908-420-3759 weekdays or, email us: info@fountainhealthcarellc.com

PRINCIPAL DISPLAY PANEL - 105 g Tube Carton

NDC 69297-000-19

Oral 7®Xylitol
balancing your mouth's natural flora

Beneficial for the
whole family!

✓ No SLS (harsh drying detergent)
✓ With Fluoride & Calcium
✓ Extra Beneficial for Dry Mouth

MOISTURIZING
TOOTHPASTE

With natural enzymes to
help reinforce your
mouth's own defense system

75mL (105g) e